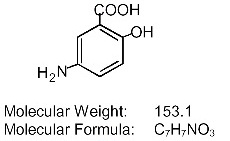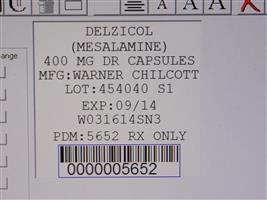 DRUG LABEL: Delzicol
NDC: 68151-5652 | Form: CAPSULE, DELAYED RELEASE
Manufacturer: Carilion Materials Management
Category: prescription | Type: HUMAN PRESCRIPTION DRUG LABEL
Date: 20160806

ACTIVE INGREDIENTS: MESALAMINE 400 mg/1 1
INACTIVE INGREDIENTS: SILICON DIOXIDE; DIBUTYL SEBACATE; FERRIC OXIDE RED; FERRIC OXIDE YELLOW; LACTOSE MONOHYDRATE; MAGNESIUM STEARATE; METHACRYLIC ACID - METHYL METHACRYLATE COPOLYMER (1:2); POLYETHYLENE GLYCOLS; POVIDONES; SODIUM STARCH GLYCOLATE TYPE A POTATO; TALC; HYPROMELLOSES

HIGHLIGHTS OF PRESCRIBING INFORMATION

These highlights do not include all the information needed to use DELZICOL® safely and effectively. See full prescribing information for DELZICOL.
DELZICOL® (mesalamine) delayed-release capsules, for oral use
Initial U.S. Approval: 1987

RECENT MAJOR CHANGES

Indications and Usage, Treatment of Mildly to Moderately Active Ulcerative Colitis (1.1) | 04/2014
Dosage and Administration, Dosage for Treatment of Mildly to Moderately Active Ulcerative Colitis (2.1) | 04/2014
Dosage and Administration, Dosage for Treatment of Mildly to Moderately Active Ulcerative Colitis (2.1) | 10/2014
Dosage and Administration, Dosage for Maintenance of Remission of Ulcerative Colitis (2.2) | 10/2014
Dosage and Administration, Important Administration Instructions (2.3) | 04/2014
Dosage and Administration, Testing Prior to DELZICOL Administration (2.4) | 04/2014

1 INDICATIONS AND USAGE

DELZICOL is an aminosalicylate indicated for:

- Treatment of mildly to moderately active ulcerative colitis in patients 12 years of age and older (1.1)

- Maintenance of remission of ulcerative colitis in adults (1.2)

2 DOSAGE AND ADMINISTRATION

- For the treatment of mildly to moderately active ulcerative colitis (2.1)
  ºAdults: 800 mg three times daily with or without food (2.4 grams/day) for 6 weeks
  º Pediatric Patients 12 years or older: Total daily dose is weight-based up to a maximum of 2.4 grams/day with or without food (see table below); twice daily dosing for 6 weeks

Weight Group (kg) | Daily Dose (mg/kg/day) | Maximum Daily Dose (grams/day)
17 to < 33 | 36 to 71 | 1.2
33 to < 54 | 37 to 61 | 2.0
54 to 90 | 27 to 44 | 2.4

- For the maintenance of remission of ulcerative colitis in adults, 1.6 g daily, in divided doses (2.2)
- Do not open, crush, break, or chew the capsules. Swallow whole with water (2.3)
- Two DELZICOL 400 mg capsules should not be substituted with one mesalamine delayed-release 800 mg tablet (2.3)
- Assess children for the ability to swallow capsules (2.3)
- Recommend that renal function be evaluated prior to initiation of DELZICOL (2.4, 5.1)

3 DOSAGE FORMS AND STRENGTHS

Delayed-release capsules: 400 mg (3)

4 CONTRAINDICATIONS

Patients with known hypersensitivity to salicylates or aminosalicylates or to any of the ingredients of DELZICOL capsules (4, 5.3)

5 WARNINGS AND PRECAUTIONS

- Renal Impairment (for example, minimal change nephropathy, acute and chronic interstitial nephritis, renal failure): Assess renal function at beginning of treatment and periodically during treatment (5.1)
- Mesalamine-induced Acute Intolerance Syndrome: Has been reported. Observe patients closely for worsening of these symptoms while on treatment (5.2)
- Hypersensitivity Reactions: Use caution when treating patients who are hypersensitive to sulfasalazine. Mesalamine-induced cardiac hypersensitivity reactions (myocarditis and pericarditis) have been reported (5.3)
- Hepatic Failure: Has been reported in patients with pre-existing liver disease. Use caution when treating patients with liver disease (5.4)
- Prolonged Gastric Retention in Patients with Upper Gastrointestinal Obstruction: May lead to a delay in onset of action (5.5)

6 ADVERSE REACTIONS

The most common adverse reactions (observed in greater than or equal to 5% of adults in clinical trials) were abdominal pain, eructation, pain, back pain, rash, dyspepsia, rhinitis, flu syndrome, asthenia, flatulence, vomiting, fever, arthralgia, constipation, and gastrointestinal bleeding (6.1)
Adverse reactions in children were similar (6.1)
To report SUSPECTED ADVERSE REACTIONS, contact Warner Chilcott at 1-800-521-8813 or FDA at 1-800-FDA-1088 or www.fda.gov/medwatch

7 DRUG INTERACTIONS

- Nephrotoxic agents including NSAIDs: Renal reactions have been reported (7.1)
- Azathioprine or 6-mercaptopurine: Blood disorders have been reported (7.2)

8 USE IN SPECIFIC POPULATIONS

- Renal Impairment: Use DELZICOL with caution in patients with a history of renal disease (5.1, 7.1, 8.6)
- Geriatric Patients: Monitor blood cell counts in geriatric patients (8.5)

FULL PRESCRIBING INFORMATION

1 INDICATIONS AND USAGE

1.1 Treatment of Mildly to Moderately Active Ulcerative Colitis

DELZICOL® (mesalamine) delayed-release capsules are indicated for the treatment of mildly to moderately active ulcerative colitis in patients 12 years of age and older.

1.2 Maintenance of Remission of Ulcerative Colitis in Adults

DELZICOL® (mesalamine) delayed-release tablets are indicated for the maintenance of remission of ulcerative colitis in adults. The safety and effectiveness of DELZICOL for the maintenance of remission of ulcerative colitis in pediatric patients have not been established.

2 DOSAGE AND ADMINISTRATION

2.1 Dosage for Treatment of Mildly to Moderately Active Ulcerative Colitis

Adults
For adults, the recommended dosage of DELZICOL is two 400 mg capsules to be taken three times daily (total daily dose of 2.4 grams), for a duration of 6 weeks [see Clinical Studies (14.1)].

Pediatrics
For pediatric patients 12 years of age and older, the recommended total daily dose of DELZICOL is weight-based (up to maximum of 2.4 grams/day). DELZICOL capsules are to be taken twice daily with or without food for a duration of 6 weeks [see Clinical Studies (14.1)].

Pediatric Dosage by Weight
Weight Group (kg) | Daily Dose (mg/kg/day) | Maximum Daily Dose (grams/day)
17 to < 33 | 36 to 71 | 1.2
33 to < 54 | 37 to 61 | 2.0
54 to 90 | 27 to 44 | 2.4

2.2 Dosage for Maintenance of Remission of Ulcerative Colitis in Adults

For the maintenance of remission of ulcerative colitis, the recommended dose of DELZICOL in adults is 1.6 g daily with or without food in divided doses [see Clinical Studies (14.2)].

2.3 Important Administration Instructions

Do not open, crush, break, or chew the capsules. Swallow whole with water.

Before prescribing DELZICOL capsules, children should be assessed for the ability to swallow capsules.

Two DELZICOL 400 mg capsules should not be substituted with one mesalamine delayed-release 800 mg tablet.

2.4 Testing Prior to DELZICOL Administration

Evaluate renal function prior to initiation of DELZICOL [see Warnings and Precautions (5.1)].

3 DOSAGE FORMS AND STRENGTHS

DELZICOL (mesalamine) delayed-release capsules are red capsules containing 400 mg mesalamine and imprinted with “WC 400mg” in white.

4 CONTRAINDICATIONS

DELZICOL is contraindicated in patients with known hypersensitivity to salicylates or aminosalicylates or to any of the ingredients of DELZICOL [see Warnings and Precautions (5.3), Adverse Reactions (6.2), and Description (11)].

5 WARNINGS AND PRECAUTIONS

5.1 Renal Impairment

Renal impairment, including minimal change nephropathy, acute and chronic interstitial nephritis, and renal failure, has been reported in patients taking products such as DELZICOL that contain mesalamine or are converted to mesalamine.

It is recommended that patients have an evaluation of renal function prior to initiation of DELZICOL and periodically while on therapy.

Prescribers should carefully evaluate the risks and benefits when using DELZICOL in patients with known renal impairment or history of renal disease [see Drug Interactions (7.1) and Nonclinical Toxicology (13.2)].

5.2 Mesalamine-Induced Acute Intolerance Syndrome

Mesalamine has been associated with an acute intolerance syndrome that may be difficult to distinguish from an exacerbation of ulcerative colitis. Although the exact frequency of occurrence has not been determined, it has occurred in 3% of controlled clinical trials of mesalamine or sulfasalazine. Symptoms include cramping, abdominal pain, bloody diarrhea, and sometimes fever, headache, and rash. Observe patients closely for worsening of these symptoms while on treatment. If acute intolerance syndrome is suspected, promptly discontinue treatment with DELZICOL.

5.3 Hypersensitivity Reactions

Some patients who have experienced a hypersensitivity reaction to sulfasalazine may have a similar reaction to DELZICOL or to other compounds that contain or are converted to mesalamine.

Mesalamine-induced cardiac hypersensitivity reactions (myocarditis and pericarditis) have been reported with DELZICOL and other mesalamine medications. Caution should be taken in prescribing this medicine to patients with conditions predisposing them to the development of myocarditis or pericarditis.

5.4 Hepatic Failure

There have been reports of hepatic failure in patients with pre-existing liver disease who have been administered mesalamine. Caution should be exercised when administering DELZICOL to patients with liver disease.

5.5 Prolonged Gastric Retention in Patients with Upper Gastrointestinal Obstruction

Organic or functional obstruction in the upper gastrointestinal tract may cause prolonged gastric retention of DELZICOL which would delay release of mesalamine in the colon.

6 ADVERSE REACTIONS

The most serious adverse reactions seen in DELZICOL clinical trials or with other products that contain or are metabolized to mesalamine are:

- Renal impairment, including renal failure [see Warnings and Precautions (5.1)]
- Acute intolerance syndrome [see Warnings and Precautions (5.2)]
- Hypersensitivity reactions [see Warnings and Precautions (5.3)]
- Hepatic failure [see Warnings and Precautions (5.4)]

The data presented in Section 6.1 are from clinical trials conducted with mesalamine delayed-release tablets. DELZICOL is bioequivalent to these mesalamine delayed-release tablets.

6.1 Clinical Trials Experience

Because clinical trials are conducted under widely varying conditions, adverse reaction rates observed in the clinical trials of a drug cannot be directly compared to rates in the clinical trials of another drug and may not reflect the rates observed in practice.

In total, mesalamine delayed-release 400 mg tablets have been evaluated in 2690 patients with ulcerative colitis in controlled and open-label trials. Adverse events presented in the following sections may occur regardless of length of therapy and similar events have been reported in short- and long-term studies and in the postmarketing setting.

Clinical studies supporting mesalamine delayed-release tablets use for the treatment of mildly to moderately active ulcerative colitis included two 6-week, placebo-controlled, randomized, double-blind studies in adults with mildly to moderately active ulcerative colitis (Studies 1 and 2), and one 6-week, randomized, double-blind, study of 2 dose levels in children with mildly to moderately active ulcerative colitis. Clinical studies supporting the use of mesalamine delayed-release tablets in the maintenance of remission of ulcerative colitis included a 6-month, randomized, double-blind, placebo-controlled, multi-center study and four active-controlled maintenance trials comparing mesalamine delayed-release with sulfasalazine. Mesalamine delayed-release tablets have been evaluated in 427 adults and 82 children with ulcerative colitis in these controlled studies.

Treatment of Mildly to Moderately Active Ulcerative Colitis in Adults

In two 6-week placebo-controlled clinical studies (Studies 1 and 2) involving 245 patients, 155 of whom were randomized to mesalamine delayed-release tablets [see Clinical Studies (14.1)], 3.2% of the mesalamine delayed-release tablets-treated patients discontinued therapy because of adverse reactions as compared to 2.2% of the placebo-treated patients. The average age of patients in Study 1 was 42 years and 48% of patients were male. The average age of patients in Study 2 was 42 years and 59% of patients were male. Adverse reactions leading to withdrawal from mesalamine delayed-release tablets included (each in one patient): diarrhea and colitis flare; dizziness, nausea, joint pain, and headache; rash, lethargy and constipation; dry mouth, malaise, lower back discomfort, mild disorientation, mild indigestion and cramping; headache, nausea, aching, vomiting, muscle cramps, a stuffy head, plugged ears, and fever.

Adverse reactions in patients treated with mesalamine delayed-release tablets occurring at a frequency of at least 2% and at a rate greater than placebo in 6-week, double-blind, placebo-controlled trials (Studies 1 and 2) are listed in Table 1 below.

Table 1: Adverse Reactions Reported in Two Six-Week Placebo-Controlled Trials (Studies 1 and 2) Experienced by at Least 2% of patients in the mesalamine delayed-release tablets Group and at a Rate Greater than Placebo
 | % of Patients with Adverse Reactions
Adverse Reaction | mesalamine delayed-release tablets | Placebo
 | (n = 152) | (n = 87)
Abdominal pain | 18 | 14
Eructation | 16 | 15
Pain | 14 | 8
Back pain | 7 | 5
Rash | 6 | 3
Dyspepsia | 6 | 1
Arthralgia | 5 | 3
Vomiting | 5 | 2
Constipation | 5 | 1
Chest pain | 3 | 2
Chills | 3 | 2
Peripheral edema | 3 | 2
Myalgia | 3 | 1
Sweating | 3 | 1
Pruritus | 3 | 0
Acne | 2 | 1
Malaise | 2 | 1
Arthritis | 2 | 0

Treatment of Mildly to Moderately Active Ulcerative Colitis in Pediatric Patients 5 to 17 Years Old

A randomized, double-blind, 6-week study of 2 dose levels of mesalamine delayed-release 400 mg tablets (Study 3) was conducted in 82 pediatric patients 5 to 17 years of age with mildly to moderately active ulcerative colitis. All patients were divided by body weight category (17 to less than 33 kg, 33 to less than 54 kg, and 54 to 90 kg) and randomly assigned to receive a low dose (1.2, 2.0, and 2.4 g/day for the respective body weight category) or a high dose (2.0, 3.6, and 4.8 g/day).

The high dose is not an approved dosage because it was not found to be more effective than the approved dose [see Dosage and Administration (2.1) and Clinical Studies (14.1)].

Duration of exposure to mesalamine among the 82 patients in the study ranged from 12 to 50 days (mean of 40 days in each dose group). The majority (88%) of patients in each group were treated for more than 5 weeks. Table 2 provides a summary of the specific reported adverse reactions (ARs).

Table 2: Adverse Reactions Reported in One Six-Week Trial (Study 3) Experienced by at Least 5% of Patients in the Low Dose Group or High Dose Group
 | % of Patients with Adverse Reactions
 | Low Dose | High Dose
Adverse Reaction | (n=41) | (n=41)
Nasopharyngitis | 15 | 12
Ulcerative Colitis | 12 | 5
Headache | 10 | 5
Abdominal pain | 10 | 2
Dizziness | 7 | 2
Sinusitis | 7 | 0
Rash | 5 | 5
Cough | 5 | 0
Diarrhea | 5 | 0
Fatigue | 2 | 10
Pyrexia | 0 | 7
Increased Lipase | 0 | 5
Low Dose = mesalamine 400 mg delayed-release tablet 1.2 - 2.4 g/day;
High Dose = mesalamine 400 mg delayed-release tablet 2.0 - 4.8 g/day.
Dosage was dependent on body weight.
Adverse Reactions reported at the 1-week telephone follow-up visit are included.

Twelve percent of the patients in the low dose group and 5% of the patients in the high dose group had serious adverse reactions (ARs). Ulcerative colitis was reported as a serious AR in one subject in each group. Other serious ARs consisted of sinusitis, abdominal pain, decreased body mass index, adenovirus infection, bloody diarrhea, sclerosing cholangitis, and pancreatitis in one subject each in the low dose group and anemia and syncope in one subject each in the high dose group.

Seven patients were withdrawn from the study because of ARs: 5 (12%) in the low dose group (ulcerative colitis, adenovirus infection, sclerosing cholangitis, pancreatitis) and 2 (5%) in the high dose group (increased amylase and increased lipase, upper abdominal pain).

In general, the nature and severity of reactions in the pediatric population was similar to those reported in adult populations of patients with ulcerative colitis.
Maintenance of Remission of Ulcerative Colitis in Adults

In a 6-month placebo-controlled maintenance trial involving 264 patients (Study 4) 177 of whom were randomized to mesalamine delayed-release tablets, six (3.4%) of the patients using mesalamine delayed-release tablets discontinued therapy because of adverse reactions, as compared to four (4.6%) of patients using placebo [see Clinical Studies (14.2)]. The average age of patients in Study 4 was 42 years and 55% of patients were male. Adverse reactions leading to study withdrawal in patients using mesalamine delayed-release tablets included (each in one patient): anxiety; headache; pruritus; decreased libido; rheumatoid arthritis; and stomatitis and asthenia.

In addition to reactions listed in Table 1, the following adverse reactions occurred in patients using mesalamine delayed-release tablets at a frequency of 2% or greater in Study 4: abdominal enlargement, gastroenteritis, gastrointestinal hemorrhage, infection, joint disorder, migraine, nervousness, paresthesia, rectal disorder, rectal hemorrhage, stool abnormalities, tenesmus, urinary frequency, vasodilation, and vision abnormalities.

In 3342 patients in uncontrolled clinical studies, the following adverse reactions occurred at a frequency of 5% or greater and appeared to increase in frequency with increasing dose: asthenia, fever, flu syndrome, pain, abdominal pain, back pain, flatulence, gastrointestinal bleeding, arthralgia, and rhinitis.

6.2 Postmarketing Experience

In addition to the adverse reactions reported above in clinical trials involving mesalamine delayed-release tablets, the adverse reactions listed below have been identified during post-approval use of mesalamine delayed-release tablets and other mesalamine-containing products. Because these reactions are reported voluntarily from a population of uncertain size, it is not always possible to reliably estimate their frequency or establish a causal relationship to drug exposure.

Body as a Whole: Neck pain, facial edema, edema, lupus-like syndrome, drug fever.

Cardiovascular: Pericarditis, myocarditis [see Warnings and Precautions (5.3)].

Gastrointestinal: Anorexia, pancreatitis, gastritis, increased appetite, cholecystitis, dry mouth, oral ulcers, perforated peptic ulcer bloody diarrhea.

Hematologic: Agranulocytosis, aplastic anemia, thrombocytopenia, eosinophilia, leukopenia, anemia, lymphadenopathy.

Musculoskeletal: Gout.

Nervous: Depression, somnolence, emotional lability, hyperesthesia, vertigo, confusion, tremor, peripheral neuropathy, transverse myelitis, Guillain-Barré syndrome.

Renal: Renal failure, interstitial nephritis, minimal change nephropathy [see Warnings and Precautions (5.1)].

Respiratory/Pulmonary: Eosinophilic pneumonia, interstitial pneumonitis, asthma exacerbation, pleuritis.

Skin: Alopecia, psoriasis, pyoderma gangrenosus, dry skin, erythema nodosum, urticaria.

Special Senses: Eye pain, taste perversion, blurred vision, tinnitus.

Urogenital: Dysuria, urinary urgency, hematuria, epididymitis, menorrhagia, reversible oligospermia.

Laboratory Abnormalities: Elevated AST (SGOT) or ALT (SGPT), elevated alkaline phosphatase, elevated GGT, elevated LDH, elevated bilirubin, elevated serum creatinine and BUN.

7 DRUG INTERACTIONS

No formal drug interaction studies have been performed using DELZICOL with other drugs. However, the following interactions between mesalamine-containing products and other drugs have been reported.

7.1 Nephrotoxic Agents, Including Non-Steroidal Anti-Inflammatory Drugs

The concurrent use of mesalamine with known nephrotoxic agents, including nonsteroidal anti-inflammatory drugs (NSAIDs) may increase the risk of renal reactions [see Warnings and Precautions (5.1)].

7.2 Azathioprine or 6-mercaptopurine

The concurrent use of mesalamine with azathioprine or 6-mercaptopurine may increase the risk for blood disorders.

8 USE IN SPECIFIC POPULATIONS

8.1 Pregnancy

Pregnancy Category B

Risk Summary
There are no adequate and well controlled studies of DELZICOL use in pregnant women. Limited published human data on mesalamine show no increase in the overall rate of congenital malformations. Some data show an increased rate of preterm birth, stillbirth, and low birth weight; however, these adverse pregnancy outcomes are also associated with active inflammatory bowel disease. Furthermore, all pregnancies, regardless of drug exposure, have a background rate of 2 to 4% for major malformations, and 15 to 20% for pregnancy loss. No evidence of fetal harm was observed in animal reproduction studies of mesalamine in rats and rabbits at oral doses approximately 1.9 times (rat) and 3.9 times (rabbit) the recommended human dose. DELZICOL should be used in pregnancy only if clearly needed.

Human Data
Mesalamine crosses the placenta. In prospective and retrospective studies of over 600 women exposed to mesalamine during pregnancy, the observed rate of congenital malformations was not increased above the background rate in the general population. Some data show an increased rate of preterm birth, stillbirth, and low birth weight, but it is unclear whether this was due to underlying maternal disease, drug exposure, or both, as active inflammatory bowel disease is also associated with adverse pregnancy outcomes.

Animal data
Reproduction studies with mesalamine were performed during organogenesis in rats and rabbits at oral doses up to 480 mg/kg/day. There was no evidence of impaired fertility or harm to the fetus. These mesalamine doses were about 1.9 times (rat) and 3.9 times (rabbit) the recommended human dose, based on body surface area.

8.3 Nursing Mothers

Mesalamine and its N-acetyl metabolite are present in human milk. In published lactation studies, maternal mesalamine doses from various oral and rectal formulations and products ranged from 500 mg to 3 g daily. The concentration of mesalamine in milk ranged from non-detectable to 0.11 mg/L. The concentration of the N-acetyl-5-aminosalicylic acid metabolite ranged from 5 to 18.1 mg/L. Based on these concentrations, estimated infant daily doses for an exclusively breastfed infant are 0 to 0.017 mg/kg/day of mesalamine and 0.75 to 2.72 mg/kg/day of N-acetyl-5-aminosalicylic acid. The developmental and health benefits of breastfeeding should be considered along with the mother’s clinical need for DELZICOL and any potential adverse effects on the breastfed child from the drug or from the underlying maternal condition. Caution should be exercised when DELZICOL is administered to a nursing woman.

8.4 Pediatric Use

The data presented in Section 8.4 are from clinical trials conducted with mesalamine 400 mg delayed-release tablets. DELZICOL is bioequivalent to these mesalamine delayed-release tablets.

The safety and effectiveness of mesalamine delayed-release 400 mg tablets in pediatric patients 5 to 17 years of age for treatment of mildly to moderately active ulcerative colitis have been established over a 6-week period. Use of mesalamine delayed-release 400 mg tablets in these age groups is supported by evidence from adequate and well controlled studies of mesalamine delayed-release 400 mg tablets in adults and a single study in pediatric patients [see Adverse Reactions (6.1), Clinical Pharmacology (12.3) and Clinical Studies (14.1)]. However, for patients less than 12 years of age, there is no age-appropriate formulation available. Therefore, DELZICOL is indicated for the treatment of mildly to moderately active ulcerative colitis for patients 12 years of age and older.

Mesalamine delayed-release 400 mg tablets was studied in a randomized, double-blind, parallel-group, 6-week treatment study of two dose levels of mesalamine delayed-release 400 mg tablets in 82 pediatric patients 5 to 17 years of age with mildly to moderately active ulcerative colitis. All patients were divided by weight category (17 to less than 33 kg, 33 to less than 54 kg, and 54 to 90 kg) and randomly assigned to receive a low dose (1.2, 2.0, and 2.4 g/day for the respective weight category) or a high dose (2.0, 3.6, and 4.8 g/day). Baseline and screening visits were followed by a treatment period of 6 weeks [see Dosage and Administration (2.1)]. The high dose was not more effective than the low dose and is not an approved dosage [see Clinical Studies (14.1)].

The safety and effectiveness of DELZICOL in pediatric patients below the age of 5 years have not been established. The safety and effectiveness of DELZICOL in the maintenance of remission of ulcerative colitis in pediatric patients have not been established.

8.5 Geriatric Use

Clinical studies of mesalamine delayed-release tablets did not include sufficient numbers of subjects aged 65 and over to determine whether they respond differently than younger subjects. Other reported clinical experience has not identified differences in response between the elderly and younger patients. In general, the greater frequency of decreased hepatic, renal, or cardiac function, and of concomitant disease or other drug therapy in elderly patients should be considered when prescribing DELZICOL. Reports from uncontrolled clinical studies and postmarketing reporting systems suggest a higher incidence of blood dyscrasias, that is, agranulocytosis, neutropenia, pancytopenia, in subjects receiving mesalamine delayed-release tablets who are 65 years or older. Caution should be taken to closely monitor blood cell counts during treatment with DELZICOL.

8.6 Renal Impairment

Mesalamine is known to be substantially excreted by the kidney, and the risk of toxic reactions to this drug may be greater in patients with impaired renal function. Because elderly patients are more likely to have decreased renal function, care should be taken when prescribing this drug therapy. It is recommended that all patients have an evaluation of renal function prior to initiation of DELZICOL therapy and periodically while on DELZICOL therapy [see Dosage and Administration (2.4) and Warnings and Precautions (5.1)].

10 OVERDOSAGE

There is no specific antidote for mesalamine overdose and treatment for suspected acute severe toxicity with DELZICOL should be symptomatic and supportive. This may include prevention of further gastrointestinal tract absorption, correction of fluid electrolyte imbalance, and maintenance of adequate renal function. DELZICOL is a pH dependent delayed-release product and this factor should be considered when treating a suspected overdose.

11 DESCRIPTION

Each DELZICOL (mesalamine) delayed-release capsule for oral administration contains 400 mg of mesalamine, an aminosalicylate. DELZICOL (mesalamine) delayed-release capsules contain acrylic based resin, Eudragit S (methacrylic acid copolymer type B, NF), which dissolves at pH 7 or greater and releases mesalamine in the terminal ileum and beyond for topical anti-inflammatory action in the colon. Mesalamine (also referred to as 5-aminosalicylic acid or 5-ASA) has the chemical name 5-amino-2-hydroxybenzoic acid. Its structural formula is:

Mesalamine structural formula

Inactive Ingredients: Each capsule contains colloidal silicon dioxide, dibutyl sebacate, ferric oxide red, ferric oxide yellow, lactose monohydrate, magnesium stearate, methacrylic acid copolymer type B (Eudragit S), polyethylene glycol, povidone, sodium starch glycolate, talc and hydroxypropyl methylcellulose (HPMC).

12 CLINICAL PHARMACOLOGY

12.1 Mechanism of Action

The mechanism of action of mesalamine is unknown, but appears to be topical rather than systemic. Mucosal production of arachidonic acid metabolites, both through the cyclooxygenase pathways, that is, prostanoids, and through the lipoxygenase pathways, that is, leukotrienes and hydroxyeicosatetraenoic acids, is increased in patients with chronic ulcerative colitis, and it is possible that mesalamine diminishes inflammation by blocking cyclooxygenase and inhibiting prostaglandin production in the colon.

12.3 Pharmacokinetics

Absorption
Approximately 28% of mesalamine in mesalamine delayed-release formulations is absorbed after oral ingestion. The Tmax for mesalamine and its metabolite, is usually delayed, reflecting the delayed-release, and ranges from 4 to 16 hours.

A high fat meal increased systemic exposure of mesalimine (geometric mean Cmax: ↑ 64%; AUC: ↑ 48%) and delayed the Tmax by 3.3 hours compared to results in the fasted state. A majority (85 - 90%) of subjects in the fed state had systemic exposures within the range noted in the fasted state, with the exception of a few that had much higher exposures due to unknown reasons. The observed differences in mesalamine exposure due to concomitant food intake are not considered to be clinically relevant at the total daily dose of 2.4 g/day. Therefore DELZICOL can be taken without regard to food.

Metabolism
The absorbed mesalamine is rapidly acetylated in the gut mucosal wall and by the liver to N-acetyl-5-aminosalicylic acid.

Excretion
Absorbed mesalamine is excreted mainly by the kidney as N-acetyl-5-aminosalicylic acid. Unabsorbed mesalamine is excreted in feces.

After intravenous administration, the elimination half-life of mesalamine is reported to be approximately 40 minutes. After oral dosing, the terminal t1/2 values for mesalamine and N-acetyl-5-aminosalicylic acid are usually about 12 hours, but are variable, ranging from 2 to 15 hours. There is a large inter-subject and intra-subject variability in the plasma concentrations of mesalamine and N-acetyl-5-aminosalicylic acid and in their terminal half-lives following administration of DELZICOL.

Specific Populations
Pediatric Patients
The pediatric data presented in Section 12 are from clinical trials conducted with mesalamine delayed-release 400 mg tablets. DELZICOL is bioequivalent to these mesalamine delayed-release tablets.

In a PK study evaluating 30, 60 and 90 mg/kg/day doses of mesalamine delayed-release 400 mg tablets administered twice daily for four weeks, the mean Cavg values of mesalamine in pediatric ulcerative colitis patients ranged from approximately 400 ng/mL to 2100 ng/mL based on data from all dose levels.

In a study in pediatric ulcerative colitis patients (Study 3), mean plasma concentrations of mesalamine (based on sparse sampling) were 820 to 988 ng/mL at the low dose level (that is, 1.2, 2.0 or 2.4 g/day based on body weight strata of 17 to less than 33 kg, 33 to less than 54 kg, and 54 to 90 kg, respectively).

13 NONCLINICAL TOXICOLOGY

13.1 Carcinogenesis, Mutagenesis, Impairment of Fertility

Carcinogenesis
Mesalamine was not carcinogenic at dietary doses of up to 480 mg/kg/day in rats and 2000 mg/kg/day in mice, which are about 2.9 and 6.1 times the maximum recommended maintenance dose of DELZICOL of 1.6 g/day or 26.7 mg/kg/day, based on 60 kg body weight, respectively, based on body surface area.

Mutagenesis
Mesalamine was negative in the Ames assay for mutagenesis, negative for induction of sister chromatid exchanges (SCE) and chromosomal aberrations in Chinese hamster ovary cells in vitro, and negative for induction of micronuclei (MN) in mouse bone marrow polychromatic erythrocytes.

Impairment of Fertility
Mesalamine, at oral doses up to 480 mg/kg/day (about 1.9 times the recommended human treatment dose on a body surface area basis), was found to have no effect on fertility or reproductive performance of male and female rats.

13.2 Animal Toxicology and/or Pharmacology

In animal studies (rats, mice, dogs), the kidney was the principal organ for toxicity. (In the following, comparisons of animal dosing to recommended human dosing are based on body surface area and a 2.4 g/day dose for a 60 kg person.)

Mesalamine causes renal papillary necrosis in rats at single doses of approximately 750 mg/kg to 1000 mg/kg (approximately 3 to 4 times the recommended human dose based on body surface area). Doses of 170 and 360 mg/kg/day (about 0.7 and 1.5 times the recommended human dose based on body surface area) given to rats for six months produced papillary necrosis, papillary edema, tubular degeneration, tubular mineralization, and urothelial hyperplasia.

In mice, oral doses of 4000 mg/kg/day mesalamine (approximately 8 times the recommended human dose based on body surface area) for three months produced tubular nephrosis, multifocal/diffuse tubulo-interstitial inflammation, and multifocal/diffuse papillary necrosis.

In dogs, single doses of 6000 mg (approximately 8 times the recommended human dose based on body surface area) of delayed-release mesalamine tablets resulted in renal papillary necrosis but were not fatal. Renal changes have occurred in dogs given chronic administration of mesalamine at doses of 80 mg/kg/day (1.1 times the recommended human dose based on body surface area).

14 CLINICAL STUDIES

The data presented in Section 14 are from clinical trials conducted with mesalamine delayed-release tablets. DELZICOL is bioequivalent to these mesalamine delayed-release tablets.

14.1 Treatment of Mildly to Moderately Active Ulcerative Colitis

Two placebo-controlled studies (Studies 1 and 2) have demonstrated the efficacy of mesalamine delayed-release tablets in patients with mildly to moderately active ulcerative colitis.

In one randomized, double-blind, multi-center trial of 158 patients (Study 1), mesalamine delayed-release doses of 1.6 g/day and 2.4 g/day for 6 weeks were compared to placebo. The scoring system for determination of treatment efficacy included assessment of stool frequency, rectal bleeding, sigmoidoscopic findings, patient’s functional assessment, and physician global assessment. At the dose of 2.4 g/day, 21 of 43 (49%) patients using mesalamine delayed-release tablets showed an improvement in sigmoidoscopic appearance of the bowel compared to 12 of 44 (27%) patients using placebo (p = 0.048). In addition, significantly more patients in mesalamine delayed-release tablets 2.4 g/day group showed improvement in rectal bleeding and stool frequency. The 1.6 g/day dose did not produce consistent evidence of effectiveness.

In a second randomized, double-blind, placebo-controlled clinical trial of 6 weeks duration in 87 (Study 2) patients, mesalamine delayed-release tablets, at a dose of 4.8 g/day, for 6 weeks, resulted in sigmoidoscopic improvement in 28 of 38 (74%) patients compared to 10 of 38 (26%) placebo patients (p less than 0.001). Also, more patients in the mesalamine delayed-release tablets 4.8 g/day group than the placebo group showed improvement in overall symptoms.

The 4.8 g/day dose is not an approved dosage for the treatment of mildly to moderately active ulcerative colitis.

Pediatrics
The safety and effectiveness of mesalamine delayed-release 400 mg tablets in pediatric patients 5 to 17 years of age for treatment of mildly to moderately active ulcerative colitis are supported by evidence from adequate and well controlled studies of mesalamine delayed-release 400 mg tablets in adults and a single study in pediatric patients.

A randomized, double-blind, 6-week study of 2 dose levels of mesalamine delayed-release 400 mg tablets (Study 3) was conducted in 82 pediatric patients 5 to 17 years of age with mildly or moderately active ulcerative colitis. All patients were divided by weight category (17 to less than 33 kg, 33 to less than 54 kg, and 54 to 90 kg) and randomly assigned to receive a low dose (1.2, 2.0, and 2.4 g/day for the respective weight category) or a high dose (2.0, 3.6, and 4.8 g/day). Doses were administered every 12 hours.

The proportion of patients who achieved success based on the Truncated Mayo Score (TM-Mayo) (based on the stool frequency and rectal bleeding subscores of the Mayo Score) and based on the Pediatric Ulcerative Colitis Activity Index (PUCAI) (which included assessment of abdominal pain, rectal bleeding, stool consistency and frequency, presence of nocturnal bowel movement and level of activity) was measured after 6 weeks of treatment. Success based on TM-Mayo was defined as either partial response (improvement from baseline in stool frequency or rectal bleeding subscores with no worsening in the other) or complete response (both stool frequency and rectal bleeding subscores equal 0). Success based on PUCAI was defined as either partial response (PUCAI reduction of greater than or equal to 20 points from Baseline to Week 6 with Week 6 score greater than or equal to 10) or complete response (PUCAI less than 10 at Week 6).

There were 41 patients in the low dose group and 41 patients in the high dose group who received at least one dose of mesalamine delayed-release 400 mg tablets; 36 patients in each dose group completed the study. Patients were considered treatment failures if they did not achieve success or dropped out due to adverse reaction or lack of efficacy.

At Week 6, 73.2% of the patients in the low dose group, and 70.0% of the patients in the high dose group achieved success based on the TM-Mayo; 34.1% of the patients in the low dose group and 42.5% of the patients in the high dose group achieved complete response. At Week 6, 56.1% of the patients in the low dose group, and 55.0% of the patients in the high dose group achieved success based on the PUCAI; 46.3% of the patients in the low dose group and 42.5% of the patients in the high dose group achieved complete response.

The high dose was not more effective than the low dose and is not an approved dosage [see Dosage and Administration (2.1)].

14.2 Maintenance of Remission of Ulcerative Colitis

A 6-month, randomized, double-blind, placebo-controlled, multi-center study (Study 4) involved 264 patients treated with mesalamine delayed-release tablets 0.8 g/day (n = 90), 1.6 g/day (n = 87), or placebo (n = 87). In the 0.8 g/day arm, patients were dosed twice daily; in the 1.6 g/day arm, patients were dosed four times daily. The proportion of patients treated with 0.8 g/day who maintained endoscopic remission was not statistically significant compared to placebo. The proportion of patients using mesalamine delayed-release tablets 1.6 g/day who maintained endoscopic remission of ulcerative colitis was in 61 of 87 (70.1%) compared with 42 of 87 (48.3%) of placebo patients (p = 0.005).

A pooled efficacy analysis of 4 maintenance trials compared mesalamine delayed-release tablets, at doses of 0.8 g/day to 2.8 g/day, in divided doses ranging from twice daily to four times per day, with sulfasalazine, at doses of 2 g/day to 4 g/day. Treatment success was seen in 59 of 98 (59%) patients using mesalamine delayed-release tablets and 70 of 102 (69%) of patients using sulfasalazine, a non-significant difference.

HOW SUPPLIED

Product: 68151-5652

NDC: 68151-5652-2 1 CAPSULE, DELAYED RELEASE in a PACKAGE

17 PATIENT COUNSELING INFORMATION

- Instruct patients to swallow the DELZICOL capsule whole with water, taking care not to open, break, crush, or chew the capsules, because the coating is an important part of the delayed-release formulation.
- Instruct patients to contact their physician if they are unable to swallow the DELZICOL capsules whole.
- Inform patients that if they are switching from a previous oral mesalamine therapy to DELZICOL they should discontinue their previous oral mesalamine therapy and follow the dosing instructions for DELZICOL. Inform patients that intact, partially intact, and/or capsule shells have been reported in the stool. Instruct patients to contact their physician if this occurs repeatedly.
- Instruct patients to protect DELZICOL from moisture. Instruct patients to close the container tightly and to leave any desiccant pouches present in the bottle along with the capsules.

Manufactured By:
Warner Chilcott Deutschland GmbH
D-64331 Weiterstadt
Germany

Marketed By:
Warner Chilcott (US), LLC
Rockaway, NJ 07866
Content Updated: October 2014
10001367